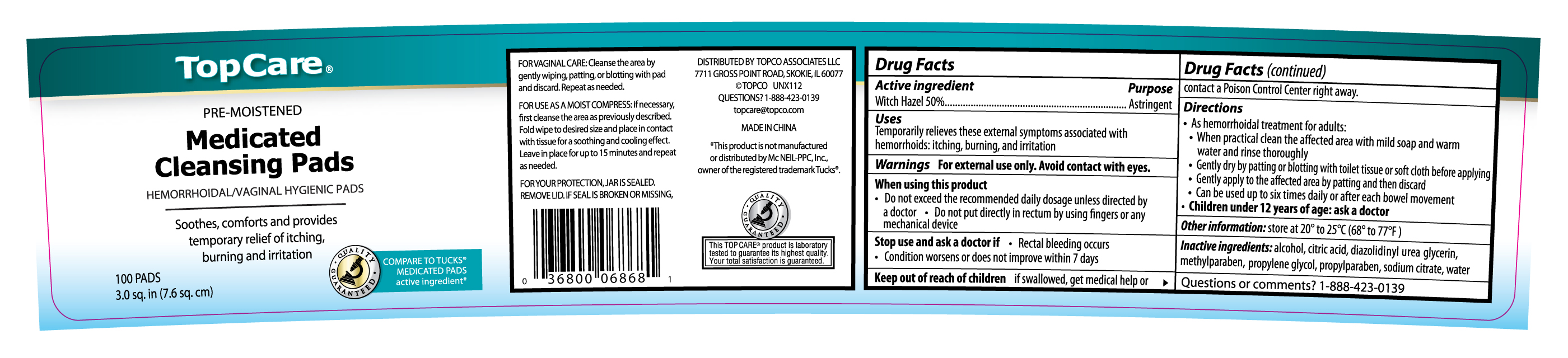 DRUG LABEL: TOPCARE MEDICATED CLEANSING PADS
NDC: 36800-068 | Form: SOLUTION
Manufacturer: TOPCO ASSOCIATES LLC
Category: otc | Type: HUMAN OTC DRUG LABEL
Date: 20120301

ACTIVE INGREDIENTS: WITCH HAZEL 0.5 mL/1 mL
INACTIVE INGREDIENTS: ALCOHOL; CITRIC ACID MONOHYDRATE; DIAZOLIDINYL UREA; GLYCERIN; METHYLPARABEN; PROPYLENE GLYCOL; PROPYLPARABEN; SODIUM CITRATE; WATER

Drug Facts

Active ingredient Purpose

Witch Hazel 50% ...............................................................Astringent

Uses

Temporarily relieves these external symptoms associated with hemorrhoids: itching, burning, and irritation

Warnings

For external use only. Avoid contact with eyes.

When using this product

- Do not exceed the recommended daily dosage unless directed by a doctor
- Do not put directly in rectum by using fingers or any mechanical device

Stop use and ask a doctor if

- Rectal bleeding occurs
- Condition worsens or does not improve within 7 days

Keep out of reach of children

If swallowed, get medical help or contact a Poison Control Center right away.

Directions

- As hemorrhoidal treatment for adults:
- When practical clean the affected area with mild soap and warm water and rinse thoroughly
- Gently dry by patting or blotting with toilet tissue or soft cloth before applying
- Gently apply to the affected area by patting and then discard
- Can be used up to six times daily or after each bowel movement
- Children under 12 years of age: ask a doctor

Other information

Store at 20o to 25oC (68o to 77oF)

INACTIVE INGREDIENT

Inactive ingredients: alcohol, citric acid, diazolidinyl urea, glycerin, methylparaben, propylene glycol, propylparaben, sodium citrate, water

DOSAGE AND ADMINISTRATION

DISTRIBUTED BY TOPCO ASSOCIATES

7711 GROSS POINT ROAD, SKOKIE, IL 60077

QUESTIONS? 1-888-423-0139

topcare@topco.com

MADE IN CHINA

PACKAGE LABEL

Enter section text here